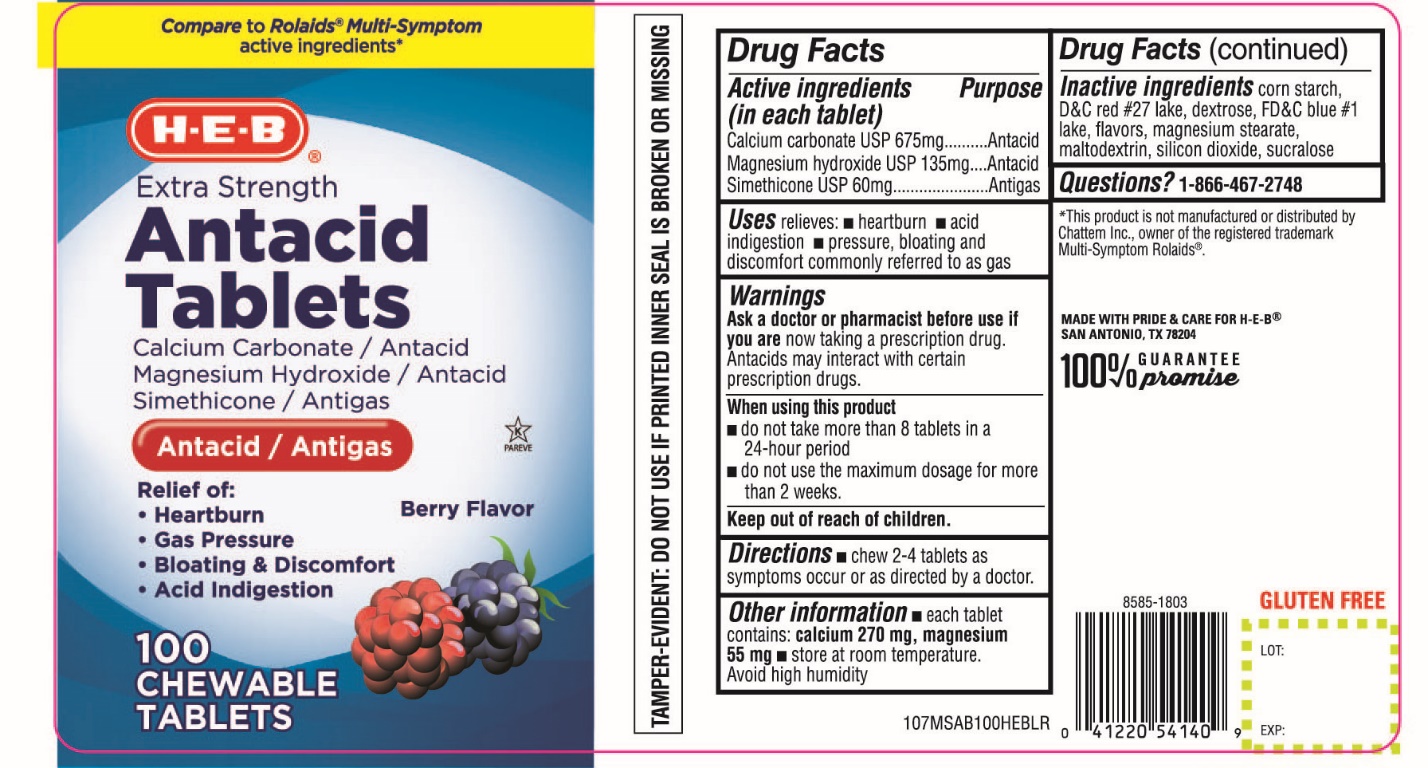 DRUG LABEL: HEB Extra Strength Antacid
NDC: 37808-701 | Form: TABLET, CHEWABLE
Manufacturer: HEB
Category: otc | Type: HUMAN OTC DRUG LABEL
Date: 20211118

ACTIVE INGREDIENTS: CALCIUM CARBONATE 675 mg/1 1; MAGNESIUM HYDROXIDE 135 mg/1 1; DIMETHICONE 60 mg/1 1
INACTIVE INGREDIENTS: STARCH, CORN; D&C RED NO. 27; DEXTROSE, UNSPECIFIED FORM; FD&C BLUE NO. 1; MAGNESIUM STEARATE; MALTODEXTRIN; SILICON DIOXIDE; SUCRALOSE

HEB Multi Symptom 100 Chewable Tablets Berry Flavor

Drug Facts

Active ingredients (in each tablet)

Calcium Carbonate USP 675 mg
Magnesium hydroxide USP 135 mg

Simethicone USP 60mg

Purpose

Antacid

Antacid

Antigas

Uses

relieves:

- heartburn
- acid indigestion
- pressure, bloating and discomfort commonly referred to as gas

Warnings

Ask a doctor or pharmacist before use if you are

now taking a prescription drug. Antacids may interact with certain prescription drugs.

When using this product

- Do not take more than 8 tablets in a 24-hour period
- Do not use the maximum dosage for more than 2 weeks

Directions

- chew 2-4 tablets completely as symptoms occur or as directed by a doctor.

Other information

- each tablet contains: calcium 270 mg, magnesium 55 mg
- Store at room temperature

Avoid high humidity

Inactive ingredients

corn starch, D&C Red No. 27, dextrose, FD&C Blue No. 1, flavor, magnesium stearate, maltodextrin, silicon dioxide, sucralose.

Questions?

1-866-467-2748

PRINCIPAL DISPLAY PANEL

NDC# 37808-701-10

Compare To Rolaids® Multi-Symptoms active ingredients*

HEB®

Extra Strength

Antacid Tablets

Calcium Carbonate/Antacid

Magnesium Hydroxide/Antacid

Simethicone/Antigas

Antacid & Anti-gas

Rapid relief of:

- Heartburn
- Gas Pressure
- Bloating & Discomfort
- Acid Indigestion

Berry Flavor

100 CHEWABLE TABLETS

MADE WITH PRIDE & CARE FOR H-E-B®

SAN ANTONIO, TX 78204

100% GURANTEE promise

*This product is not manufactured or distributed by Chattem Inc., owner of the registered trademark Multi-Symptoms ROLAIDS®

TAMPER EVIDENT: DO NOT USE IF PRINTED INNER SEAL IS BROKEN OR MISSING.